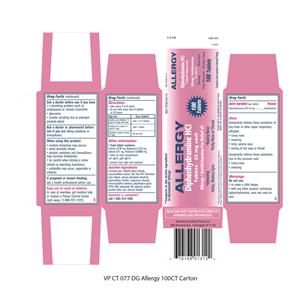 DRUG LABEL: Allergy
NDC: 76168-121 | Form: TABLET
Manufacturer: Velocity Pharma LLC
Category: otc | Type: HUMAN OTC DRUG LABEL
Date: 20180514

ACTIVE INGREDIENTS: DIPHENHYDRAMINE HYDROCHLORIDE 25 mg/1 1
INACTIVE INGREDIENTS: CARNAUBA WAX; SILICON DIOXIDE; CROSCARMELLOSE SODIUM; D&C RED NO. 27; DIBASIC CALCIUM PHOSPHATE DIHYDRATE; HYPROMELLOSES; MAGNESIUM STEARATE; CELLULOSE, MICROCRYSTALLINE; POLYETHYLENE GLYCOL 400; POLYSORBATE 80; TITANIUM DIOXIDE

DIPHENHYDRAMINE HCl 25mg, USP

Active Ingredient

(in each tablet)

Diphenhydramine HCl 25 mg

Purpose

Antihistamine

Uses

temporarily relieves these symptoms of hay fever or other upper respiratory allergies:

- runny nose
- itching of the nose or throat
- sneezing
- itchy, watery eyes
  temporarily relieves these symptoms due to the common cold:
- runny nose
- sneezing

Warnings

Do not use

- to make a child sleepy
- with any other product containing diphenhydramine, even one used on skin
  Ask a doctor before use if you have
- glaucoma
- trouble urinating due to an enlarged prostate gland
- a breathing problem such as emphysema or chronic bronchitis
  Ask a doctor or pharmacist before use if you are taking sedatives or tranquilizers
  When using this product
- you may get very drowsy
- avoid alcoholic drinks
- alcohol, sedatives & tranquilizers may increase drowsiness
- be careful when driving a motor vehicle or operating machinery
- excitability may occur, especially in children
  If pregnant or breast-feeding, ask a health professional before use.

Keep out of reach of children.

In case of overdose, get medical help or contact a Poison Control Center right away. (1-800-222-1222)

Directions

- adults and children 12 years and over : take 1-2 tablets every 4 to 6 hours; not more than 6 doses in 24 hours
- children under 12 years: ask a doctor

Other Information

- save carton for full directions and warnings
- store at 25°C(77 °F) excusrsions permitted between 15°-30°C (59°-86°F)
- this product contains 100.75 milligrams of calcium.
- Do not use if imprinted safety seal under cap is broken or missing

Inactive Ingredients

Carnauba Wax, Colloidal silion dioxide, croscarmellose sodium, D&C red #27 al lake, dibasic calcium phosphate dihydrate, hypromellose, magnesium stearate, microcrystalline cellulose, polyethylene glycol (PEG) 400, polysorbate 80,Titanium Dioxide

Questions or Comments

Call 1-855-314-1850

READ AND KEEP CARTON FOR COMPLETE WARNING AND INFORMATION